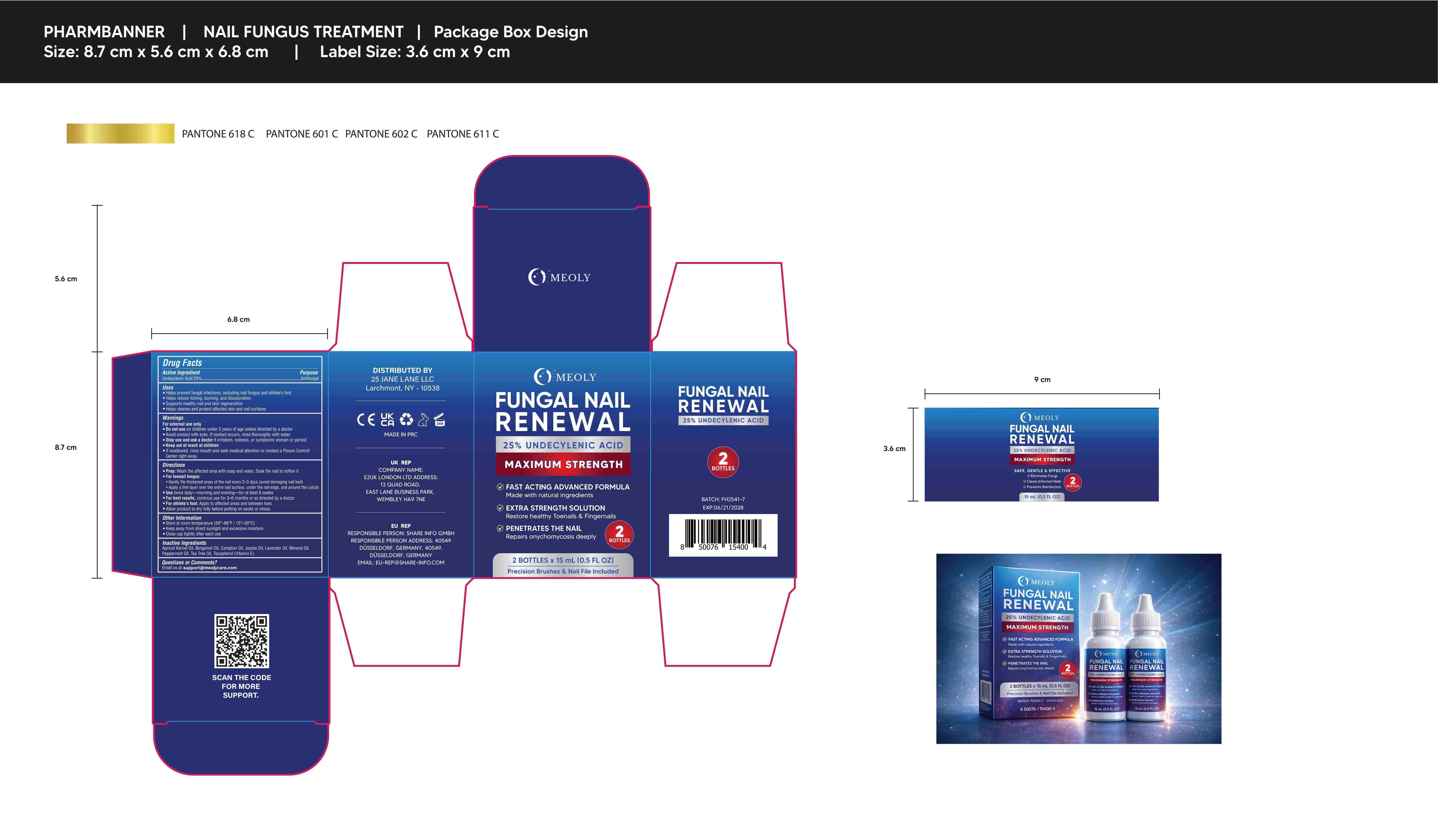 DRUG LABEL: MEOLY Fungal Nail Renewal
NDC: 83818-026 | Form: LIQUID
Manufacturer: Shenzhen Xinxin Yunhai Technology Co., Ltd.
Category: otc | Type: HUMAN OTC DRUG LABEL
Date: 20260116

ACTIVE INGREDIENTS: UNDECYLENIC ACID 25 g/100 mL
INACTIVE INGREDIENTS: TOCOPHEROL; JOJOBA OIL; BERGAMOT OIL; MINERAL OIL; PEPPERMINT OIL; CAMPHOR OIL; LAVENDER OIL; APRICOT KERNEL OIL; TEA TREE OIL

83818-026

Active Ingredient

Undecylenic Acid 25%

Purpose

Toenail Fungus treatment

Use

▪ Helps prevent fungal infections, including nail fungus and athlete's foot
▪ Helps reduce itching, burning, and discoloration
• Supports healthy nail and skin regeneration
▪ Helps cleanse and protect affected skin and nail surfaces

Warnings

For external use only
• Do not use on children under 2 years of age unless directed by a doctor
■ Avoid contact with eyes. If contact occurs, rinse thoroughly with water
Purpose ....Antifungal
▪ Stop use and ask a doctor if irritation, redness, or symptoms worsen or persist
■ Keep out of reach of children
■ If swallowed, rinse mouth and seek medical attention or contact a Poison Control
Center right away.

Do not use on children under 2 years of age unless directed by a doctor

When Using

Avoid contact with eyes. If contact occurs, rinse thoroughly with water

Stop Use

if irritation, redness, or symptoms worsen or persist

Ask Doctor

irritation, redness, or symptoms worsen or persist

Keep Out Of Reach Of Children

Directions

Wash the affected area with soap and water. Soak the nail to soften it

Other information

Store at room temperature (59°-86°F/15°-30°C)
▪ Keep away from direct sunlight and excessive moisture
Close cap tightly after each use

Inactive ingredients

Apricot Kernel Oil, Bergamot Oil, Camphor Oil, Jojoba Oil, Lavender Oil, Mineral Oil, Peppermint Oil, Tea Tree Oil, Tocopherol (Vitamin E)

Questions

email us at support@meolycare.com